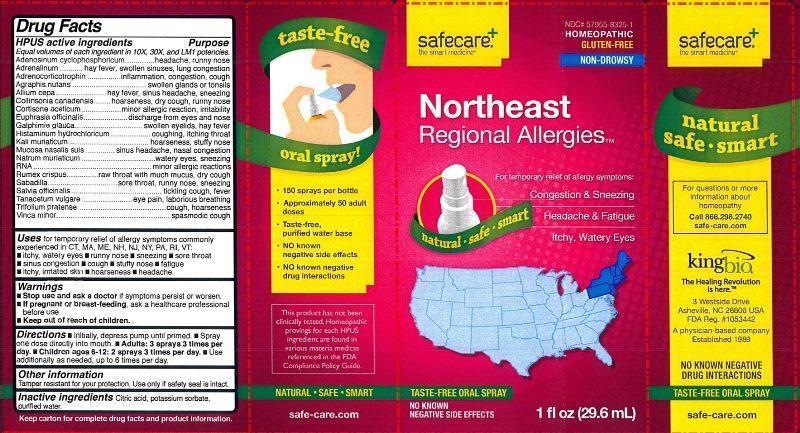 DRUG LABEL: Northeast Regional Allergies
NDC: 57955-8325 | Form: LIQUID
Manufacturer: King Bio Inc.
Category: homeopathic | Type: HUMAN OTC DRUG LABEL
Date: 20131104

ACTIVE INGREDIENTS: ADENOSINE CYCLIC PHOSPHATE 10 [hp_X]/29.6 mL; EPINEPHRINE 10 [hp_X]/29.6 mL; CORTICOTROPIN 10 [hp_X]/29.6 mL; HYACINTHOIDES NON-SCRIPTA 10 [hp_X]/29.6 mL; ONION 10 [hp_X]/29.6 mL; COLLINSONIA CANADENSIS ROOT 10 [hp_X]/29.6 mL; CORTISONE ACETATE 10 [hp_X]/29.6 mL; EUPHRASIA STRICTA 10 [hp_X]/29.6 mL; GALPHIMIA GLAUCA FLOWERING TOP 10 [hp_X]/29.6 mL; HISTAMINE DIHYDROCHLORIDE 10 [hp_X]/29.6 mL; POTASSIUM CHLORIDE 10 [hp_X]/29.6 mL; SUS SCROFA NASAL MUCOSA 10 [hp_X]/29.6 mL; SODIUM CHLORIDE 10 [hp_X]/29.6 mL; SACCHAROMYCES CEREVISIAE RNA 10 [hp_X]/29.6 mL; RUMEX CRISPUS ROOT 10 [hp_X]/29.6 mL; SCHOENOCAULON OFFICINALE SEED 10 [hp_X]/29.6 mL; SAGE 10 [hp_X]/29.6 mL; TANACETUM VULGARE TOP 10 [hp_X]/29.6 mL; TRIFOLIUM PRATENSE FLOWER 10 [hp_X]/29.6 mL; VINCA MINOR 10 [hp_X]/29.6 mL
INACTIVE INGREDIENTS: CITRIC ACID MONOHYDRATE; POTASSIUM SORBATE; WATER

Northeast Regional Allergies™

Drug Facts

____________________________________________________________________________________________________________

Equal volumes of each ingredient in 10X, 30X, and LM1 potencies.

HPUS active ingredients: Adenosinum cyclophosphoricum, Adrenalinum, Adrenocorticotrophin, Agraphis nutans, Allium cepa, Collinsonia canadensis, Cortisone aceticum, Euphrasia officinalis, Galphimia glauca, Histaminum hydrochloricum, Kali muriaticum, Mucosa nasalis suis, Natrum muriaticum, RNA, Rumex crispus, Sabadilla, Salvia officinalis, Tanacetum vulgare, Trifolium pratense, Vinca minor.

INDICATIONS AND USAGE

Uses for temporary relief of allergy symptoms commonly experienced in CT, MA, ME, NH, NJ, NY, PA, RI, VT:

- itchy, watery eyes
- runny nose
- sneezing
- sore throat
- sinus congestion
- cough
- stuffy nose
- fatigue
- itchy, irritated skin
- hoarseness
- headache

Warnings

- Stop use and ask a doctor if symptoms persist or worsen.
- If pregnant or breast-feeding, ask a healthcare professional before use.

- Keep out of reach of children.

Directions:

- Initially, depress pump until primed.
- Spray one dose directly into mouth.
- Adults: 3 sprays 3 times per day.
- Children ages 6-12: 2 sprays 3 times per day.
- Use additionally as needed, up to 6 times per day.

OTHER SAFETY INFORMATION

Tamper resistant for your protection. Use only if safety seal is intact.

Inactive Ingredients: Citric acid, potassium sorbate, purified water.

Drug Facts

__________________________________________________________________________________________________________________

HPUS active ingredients Purpose

Equal volumes of each ingredient in 10X, 30X, and LM1 potencies.

Adenosinum cyclophosphoricum....................................................headache, runny nose

Adrenalinum...............................................................................hay fever, swollen sinuses, lung congestion

Adrenocorticotrophin....................................................................inflammation, congestion, cough

Agraphis nutans..........................................................................swollen glands or tonsils

Allium cepa.................................................................................hay fever, sinus headache, sneezing

Collinsonia canadensis..................................................................hoarseness, dry cough, runny nose

Cortisone aceticum.......................................................................minor allergic reaction, irritability

Euphrasia officinalis......................................................................discharge from eyes and nose

Galphimia glauca.........................................................................swollen eyelids, hay fever

Histaminum hydrochloricum..........................................................coughing, itching throat

Kali muriaticum...........................................................................hoarseness, stuffy nose

Mucosa nasalis suis......................................................................sinus headache, nasal congestion

Natrum muriaticum......................................................................watery eyes, sneezing

RNA...........................................................................................minor allergic reactions

Rumex crispus............................................................................raw throat with much mucus, dry cough

Sabadilla....................................................................................sore throat, runny nose, sneezing

Salvia officinalis...........................................................................tickling cough, fever

Tanacetum vulgare......................................................................eye pain, laborious breathing

Trifolium pratense........................................................................cough, hoarseness

Vinca minor.................................................................................spasmodic cough